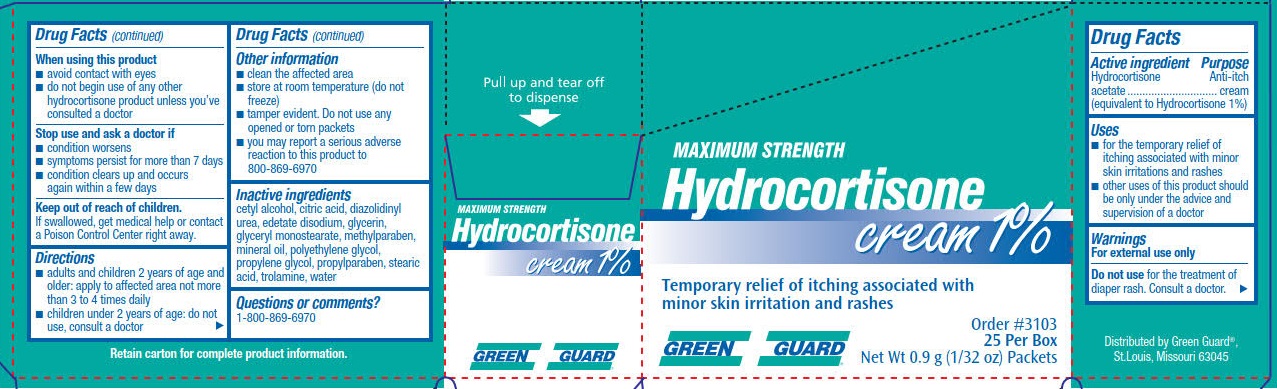 DRUG LABEL: Green Guard Hydrocortisone 1%
NDC: 47682-398 | Form: CREAM
Manufacturer: Unifirst First Aid Corporation
Category: otc | Type: HUMAN OTC DRUG LABEL
Date: 20240117

ACTIVE INGREDIENTS: HYDROCORTISONE ACETATE 10 mg/1 g
INACTIVE INGREDIENTS: TROLAMINE; CETYL ALCOHOL; CITRIC ACID MONOHYDRATE; EDETATE DISODIUM; METHYLPARABEN; GLYCERYL MONOSTEARATE; DIAZOLIDINYL UREA; POLYETHYLENE GLYCOL, UNSPECIFIED; PROPYLENE GLYCOL; PROPYLPARABEN; MINERAL OIL; STEARIC ACID; WATER; GLYCERIN

Green Guard Maximum Strength Hydrocortisone Cream 1%

Drug Facts

Active ingredient

Hydrocortisone acetate (equivalent to Hydrocortisone 1 %)

Purpose

Anti-itch cream

Uses

- for the temporary relief of itching associated with minor skin irritations and rashes
- other uses of this product should be only under the advice and supervision of a doctor

Warnings

For external use only.

Do not use for the treatment of diaper rash. Consult a doctor.

When using this product

- avoid contact with eyes
- do not begin use of any other hydrocortisone product unless you've consulted a doctor

Stop use and ask a doctor if

- condition worsens
- symptoms persist for more than 7 days
- condition clears up and occurs again within a few days

Keep out of reach of children.

If swallowed, get medical help or contact a Poison Control Center right away.

Directions

- adults and children 2 years of age and older: apply to the affected area not more than 3 to 4 times daily
- children under 2 years of age: do not use, consult a doctor

Other information

- clean the affected area
- store at room temperature (do not freeze)
- tamper evident. Do not use any opened or torn packets
- you may report a serious adverse reaction to this product to 800-634-7680

Inactive ingredients

cetyl alcohol, citric acid, diazolidinyl urea, edetate disodium, glycerin, glyceryl monostearate, methylparaben, mineral oil, polyethylene glycol, propylene glycol, propylparaben, stearic acid, trolamine, water

Questions or comments? 1-800-869-6970

PACKAGE LABEL

Maximum Strength

Hydrocortisone cream 1%

Temporary relief of itching associated with minor skin irritations and rashes

Green Guard

Order #3101

0.9 g packets 25 per box